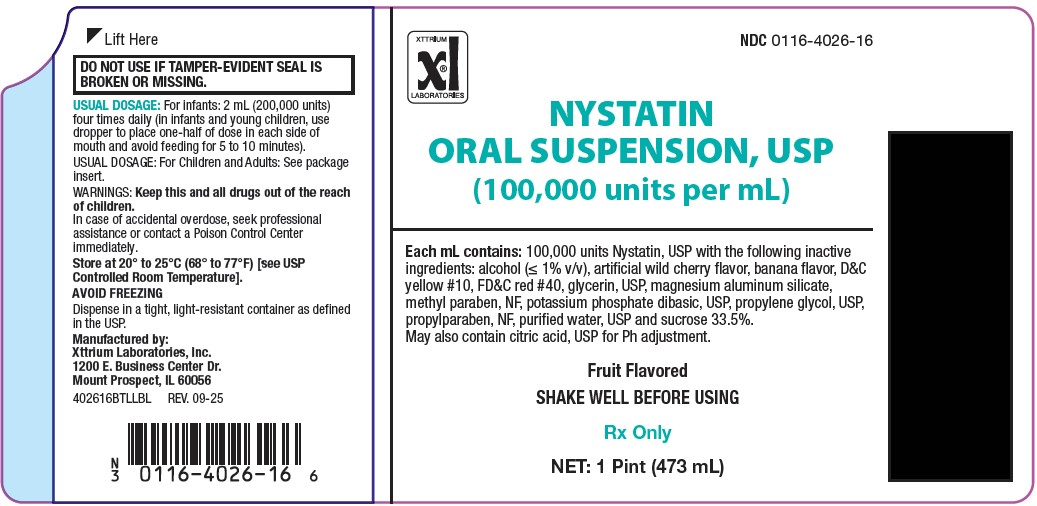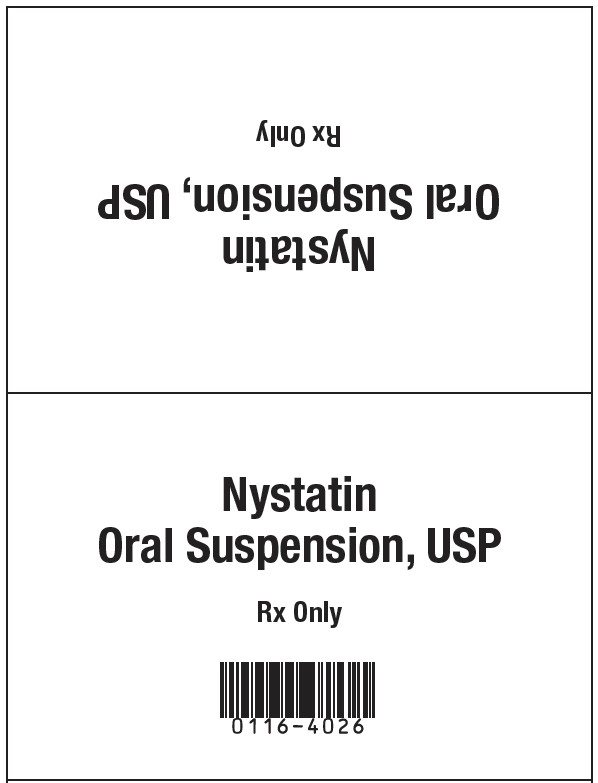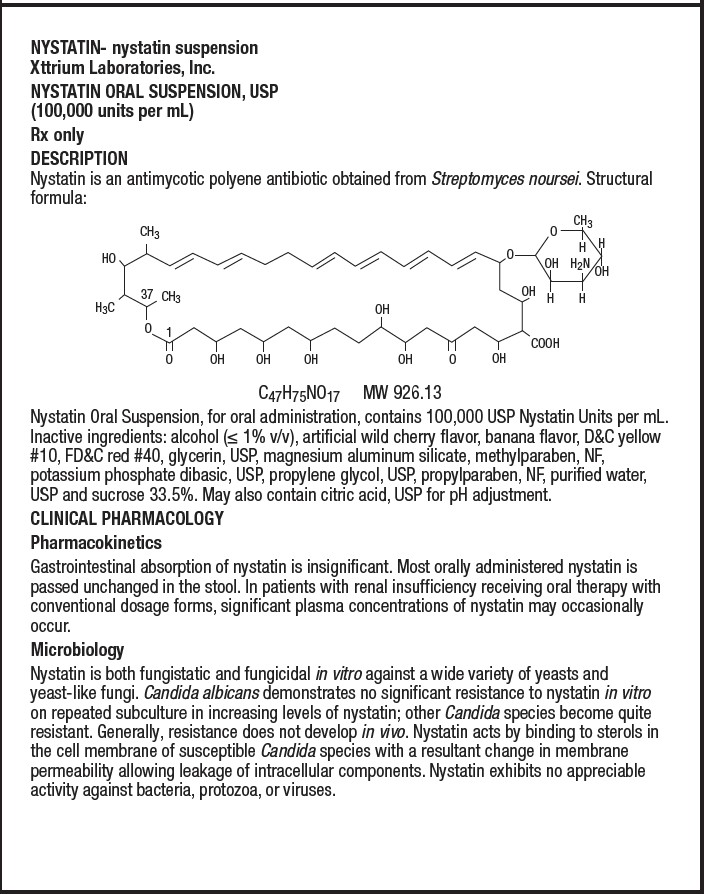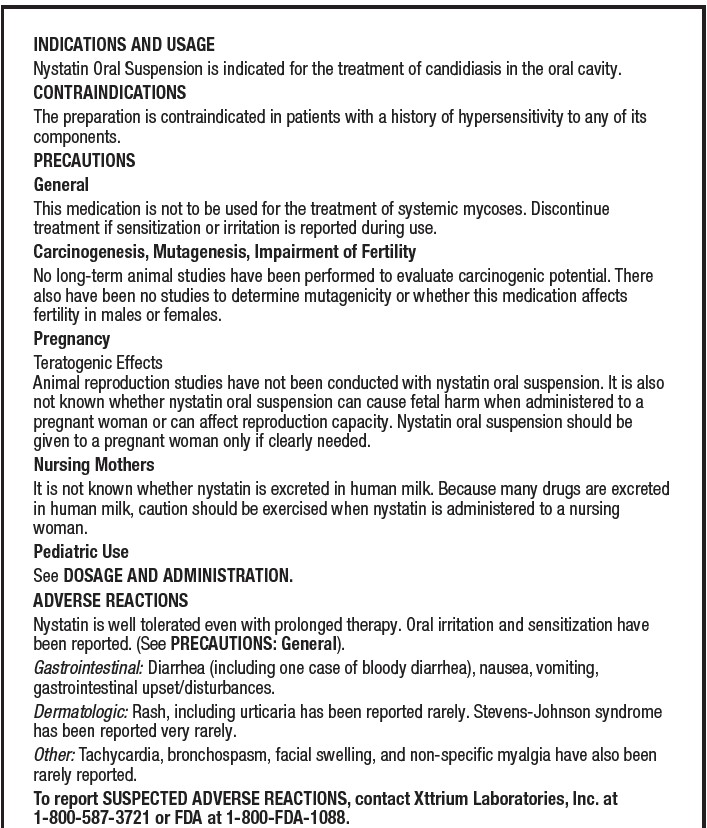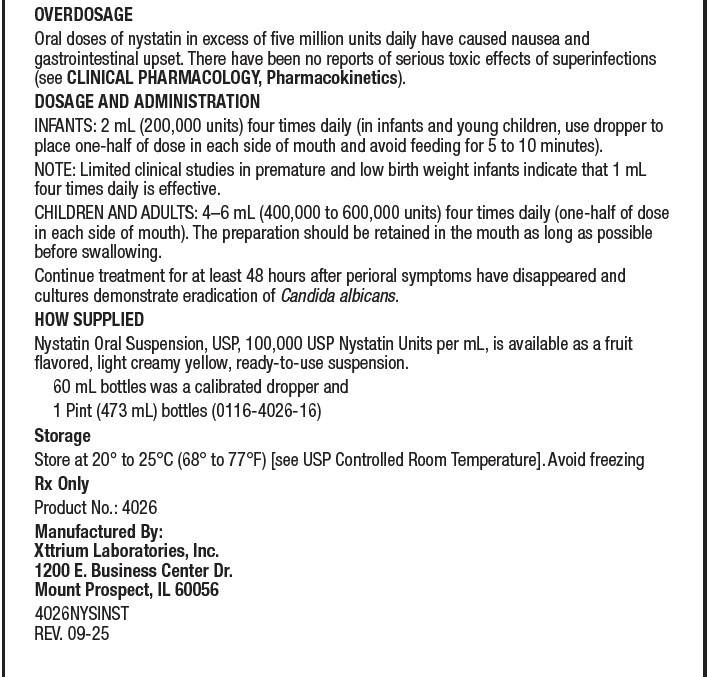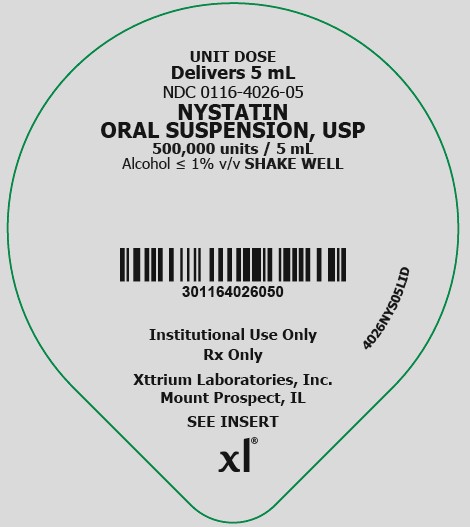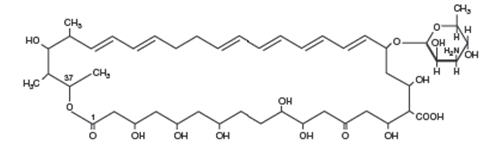 DRUG LABEL: Nystatin Oral Suspension
NDC: 0116-4026 | Form: SUSPENSION
Manufacturer: Xttrium Laboratories, Inc.
Category: prescription | Type: HUMAN PRESCRIPTION DRUG LABEL
Date: 20260206

ACTIVE INGREDIENTS: NYSTATIN 100000 [USP'U]/1 mL
INACTIVE INGREDIENTS: SUCROSE; ALCOHOL; ANHYDROUS CITRIC ACID; D&C YELLOW NO. 10; FD&C RED NO. 40; GLYCERIN; METHYLPARABEN; POTASSIUM PHOSPHATE, DIBASIC; PROPYLENE GLYCOL; PROPYLPARABEN; WATER; MAGNESIUM ALUMINUM SILICATE; CHERRY; BANANA

Nystatin Oral Suspension USP
[100,000 units per mL]

Rx Only

DESCRIPTION

Nystatin is an antimycotic polyene antibiotic obtained from Streptomyces noursei.

Structural formula:

C47H75NO17 MW 926.13

Nystatin Oral Suspension USP, for oral administration, contains 100,000 USP Nystatin Units per mL. Inactive ingredients: alcohol (≤ 1% v/v), artificial wild cherry flavor, banana flavor, D&C Yellow #10, FD&C Red #40, glycerin, USP, magnesium aluminum silicate, methylparaben, NF, potassium phosphate dibasic, USP, propylene glycol, USP, propylparaben, NF, purified water, USP and sucrose 33.5%. May also contain citric acid, USP for pH adjustment.

CLINICAL PHARMACOLOGY

Pharmacokinetics

Gastrointestinal absorption of nystatin is insignificant. Most orally administered nystatin is passed unchanged in the stool. In patients with renal insufficiency receiving oral therapy with conventional dosage forms, significant plasma concentrations of nystatin may occasionally occur.

Microbiology

Nystatin is both fungistatic and fungicidal in vitro against a wide variety of yeasts and yeast-like fungi. Candida albicans demonstrates no significant resistance to nystatin in vitro on repeated subculture in increasing levels of nystatin; other Candida species become quite resistant. Generally, resistance does not develop in vivo. Nystatin acts by binding to sterols in the cell membrane of susceptible Candida species with a resultant change in membrane permeability allowing leakage of intracellular components. Nystatin exhibits no appreciable activity against bacteria, protozoa, or viruses.

INDICATIONS AND USAGE

Nystatin Oral Suspension is indicated for the treatment of candidiasis in the oral cavity.

CONTRAINDICATIONS

The preparation is contraindicated in patients with a history of hypersensitivity to any of its components.

PRECAUTIONS

General

This medication is not to be used for the treatment of systemic mycoses. Discontinue treatment if sensitization or irritation is reported during use.

Carcinogenesis, Mutagenesis, Impairment of Fertility

No long-term animal studies have been performed to evaluate carcinogenic potential. There also have been no studies to determine mutagenicity or whether this medication affects fertility in males or females.

Pregnancy

Teratogenic Effects

Animal reproduction studies have not been conducted with nystatin oral suspension. It is also not known whether nystatin oral suspension can cause fetal harm when administered to a pregnant woman or can affect reproduction capacity. Nystatin oral suspension should be given to a pregnant woman only if clearly needed.

Nursing Mothers

It is not known whether nystatin is excreted in human milk. Because many drugs are excreted in human milk, caution should be exercised when nystatin is administered to a nursing woman.

Pediatric Use

See DOSAGE AND ADMINISTRATION.

ADVERSE REACTIONS

Nystatin is well tolerated even with prolonged therapy. Oral irritation and sensitization have been reported. (See PRECAUTIONS: General).

Gastrointestinal:Diarrhea (including one case of bloody diarrhea), nausea, vomiting, gastrointestinal upset/disturbances.

Dermatologic:Rash, including urticaria has been reported rarely. Stevens-Johnson syndrome has been reported very rarely.

Other:Tachycardia, bronchospasm, facial swelling, and non-specific myalgia have also been rarely reported.

To report SUSPECTED ADVERSE REACTIONS, contact Xttrium Laboratories, Inc. at 1-800-587-3721 or FDA at 1-800-FDA-1088 or www.fda.gov/medwatch.

OVERDOSAGE

Oral doses of nystatin in excess of five million units daily have caused nausea and gastrointestinal upset. There have been no reports of serious toxic effects of superinfections (See CLINICAL PHARMACOLOGY, Pharmacokinetics).

DOSAGE AND ADMINISTRATION

INFANTS: 2 mL (200,000 units) four times daily (in infants and young children, use dropper to place one-half of dose in each side of mouth and avoid feeding for 5 to 10 minutes).

NOTE: Limited clinical studies in premature and low birth weight infants indicate that 1 mL four times daily is effective.

CHILDREN AND ADULTS: 4-6 mL (400,000 to 600,000 units) four times daily (one-half of dose in each side of mouth). The preparation should be retained in the mouth as long as possible before swallowing.

Continue treatment for at least 48 hours after perioral symptoms have disappeared and cultures demonstrate eradication of Candida albicans.

HOW SUPPLIED

Nystatin Oral Suspension USP, 100,000 USP Nystatin Units per mL, is available as a fruit flavored, light creamy yellow, ready-to-use suspension.

60 mL bottle was a calibrated dropper and

1 Pint (473 mL) bottles (0116-4026-16)

Storage

Store at 20° to 25°C (68° to 77°F) [See USP Controlled Room Temperature].

Avoid freezing.

Rx Only
Product No.: 4026
Manufactured By:
Xttrium Laboratories, Inc.
1200 E. Business Center Dr.
Mount Prospect, IL 60056
402616BTLLBL
REV. 09-25

PRINCIPAL DISPLAY PANEL - 60 mL Bottle Label

NDC 0116-4026-16

NYSTATIN ORAL SUSPENSION, USP

(100,000 units per mL)

Each mL contains: 100,000 units Nystatin, USP with the following inactive ingredients: alcohol (≤ 1% v/v), artificial wild cherry flavor, banana flavor, D&C yellow #10, FD&C red #40, glycerin, USP, magnesium aluminum silicate, methyl paraben, NF, potassium phosphate dibasic, USP, propylene glycol, USP, propylparaben, NF, purified water, USP and sucrose 33.5%.
May also contain citric acid, USP for Ph adjustment.
Fruit Flavored
SHAKE WELL BEFORE USING
Rx Only
NET: 1 Pint (473 mL)

USUAL DOSAGE: For infants: 2 mL (200,000 units) four times daily (in infants and young children, use dropper to place one-half of dose in each side of mouth and avoid feeding for 5 to 10 minutes).
USUAL DOSAGE: For Children and Adults: See package insert.
WARNINGS: Keep this and all drugs out of the reach of children.
In case of accidental overdose, seek professional assistance or contact a Poison Control Center immediately.
Store at 20° to 25°C (68° to 77°F) [see USP Controlled Room Temperature].
AVOID FREEZING
Dispense in a tight, light-resistant container as defined in the USP.
Manufactured by:
Xttrium Laboratories, Inc.
1200 E. Business Center Dr.
Mount Prospect, IL 60056
402616BTLLBL REV. 09-25

PRINCIPAL DISPLAY PANEL - 5 mL Unit Dose Cup Label

UNIT DOSE

Delivers 5 mL
NDC 0116-4026-05
NYSTATIN
ORAL SUSPENSION, USP
500,000 units / 5 mL
Alcohol ≤ 1% v/v SHAKE WELL

Institutional Use Only

Rx Only

Xttrium Laboratories, Inc.

Mount Prospect, IL

SEE INSERT